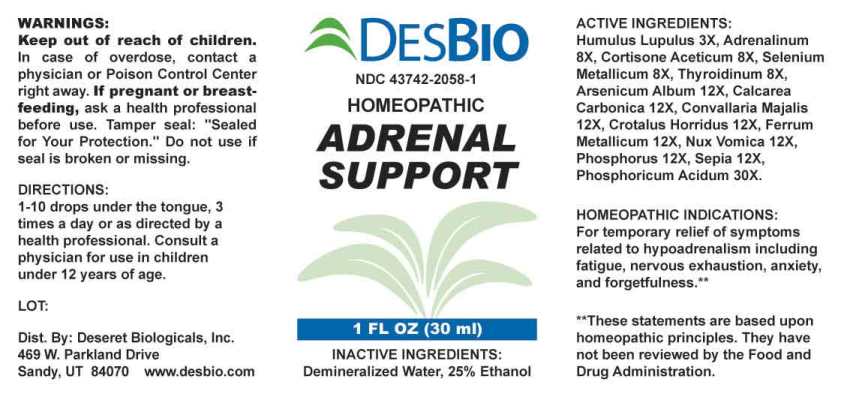 DRUG LABEL: Adrenal Support
NDC: 43742-2058 | Form: LIQUID
Manufacturer: Deseret Biologicals, Inc.
Category: homeopathic | Type: HUMAN OTC DRUG LABEL
Date: 20221109

ACTIVE INGREDIENTS: HOPS 3 [hp_X]/1 mL; EPINEPHRINE 8 [hp_X]/1 mL; CORTISONE ACETATE 8 [hp_X]/1 mL; SELENIUM 8 [hp_X]/1 mL; THYROID, PORCINE 8 [hp_X]/1 mL; ARSENIC TRIOXIDE 12 [hp_X]/1 mL; OYSTER SHELL CALCIUM CARBONATE, CRUDE 12 [hp_X]/1 mL; CONVALLARIA MAJALIS 12 [hp_X]/1 mL; CROTALUS HORRIDUS HORRIDUS VENOM 12 [hp_X]/1 mL; IRON 12 [hp_X]/1 mL; STRYCHNOS NUX-VOMICA SEED 12 [hp_X]/1 mL; PHOSPHORUS 12 [hp_X]/1 mL; SEPIA OFFICINALIS JUICE 12 [hp_X]/1 mL; PHOSPHORIC ACID 30 [hp_X]/1 mL
INACTIVE INGREDIENTS: WATER; ALCOHOL

DRUG FACTS:

ACTIVE INGREDIENTS:

Humulus Lupulus 3X, Adrenalinum 8X, Cortisone Aceticum 8X, Selenium Metallicum 8X, Thyroidinum (Suis) 8X, Arsenicum Album 12X, Calcarea Carbonica 12X, Convallaria Majalis 12X, Crotalus Horridus 12X, Ferrum Metallicum 12X, Nux Vomica 12X, Phosphorus 12X, Sepia 12X, Phosphoricum Acidum 30X.

HOMEOPATHIC INDICATIONS:

For temporary relief of symptoms related to hypoadrenalism including fatigue, nervous exhaustion, anxiety, and forgetfulness.**

**These statements are based upon homeopathic principles. They have not been reviewed by the Food and Drug Administration.

WARNINGS:

Keep out of reach of children. In case of overdose, contact a physician or Poison Control Center right away.

If pregnant or breast-feeding, ask a health professional before use.

Tamper seal: "Sealed for Your Protection." Do not use if seal is broken or missing.

Keep out of reach of children. In case of overdose, contact a physician or Poison Control Center right away.

DIRECTIONS:

1-10 drops under the tongue, 3 times a day or as directed by a health professional. Consult a physician for use in children under 12 years of age.

HOMEOPATHIC INDICATIONS:

For temporary relief of symptoms related to hypoadrenalism including fatigue, nervous exhaustion, anxiety, and forgetfulness.**

**These statements are based upon homeopathic principles. They have not been reviewed by the Food and Drug Administration.

INACTIVE INGREDIENTS:

Demineralized Water, 25% Ethanol

QUESTIONS:

Dist. By: Deseret Biologicals, Inc.

469 W. Parkland Drive

Sandy, UT 84070 www.desbio.com

PACKAGE LABEL DISPLAY:

DESBIO

NDC 43742-2058-1

HOMEOPATHIC

ADRENAL

SUPPORT

1 FL OZ (30 ml)